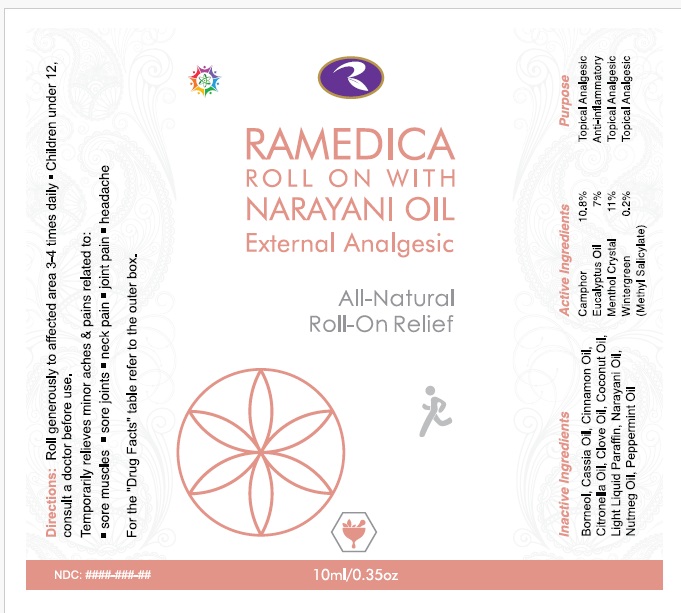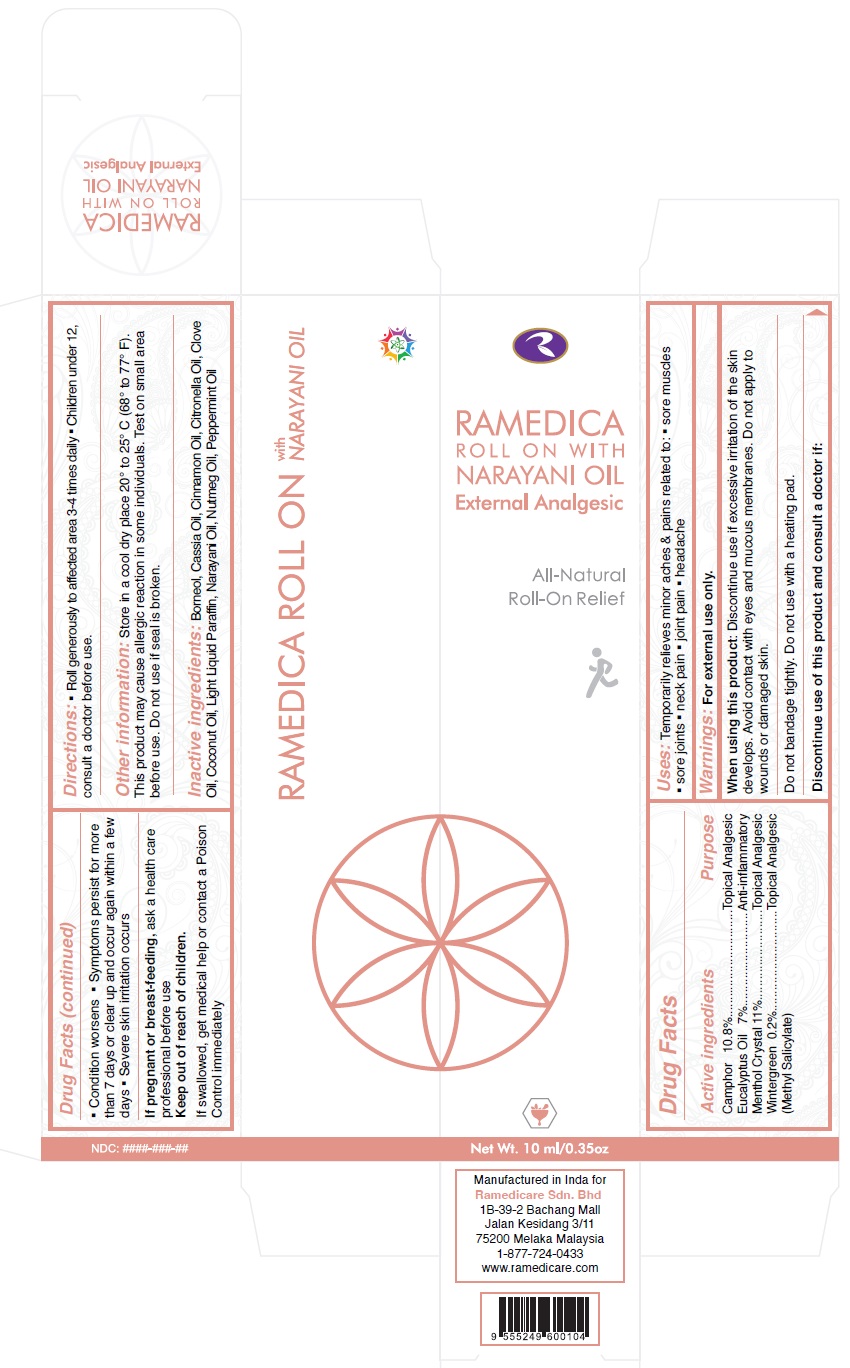 DRUG LABEL: Ramedica Roll On
NDC: 66059-0003 | Form: OIL
Manufacturer: Ramedicare Sdn. Bhd.
Category: otc | Type: HUMAN OTC DRUG LABEL
Date: 20241118

ACTIVE INGREDIENTS: CAMPHOR (NATURAL) 10.8 g/100 mL; METHYL SALICYLATE 0.2 g/100 mL; EUCALYPTUS OIL 7 g/100 mL; MENTHOL 11 g/100 mL
INACTIVE INGREDIENTS: BORNEOL; CHINESE CINNAMON OIL; CINNAMON OIL; CITRONELLA OIL; CLOVE OIL; COCONUT OIL; MINERAL OIL; PEPPERMINT OIL

Active Ingredients

Camphor 10.8%

Wintergreen Oil (Methyl Salicylate) 0.2%

Eucalyptus Oil 7%

Menthol 11%

Purpose

Camphor 10.8%................................Topical Analgesic
Eucalyptus Oil 7%...........................Anti-inflammatory
Menthol Crystal 11%.........................Topical Analgesic
Wintergreen 0.2%.............................Topical Analgesic
(Methyl Salicylate)

Uses

Temporarily relieves minor aches & pains related to

- sore muscles
- sore joints
- neck pain
- joint pain
- headache

Warnings

For external use only.
When using this product: Discontinue use if excessive irritation of the skin develops. Avoid contact with eyes and mucous membranes. Do not apply to wounds or damaged skin. Do not bandage tightly. Do not use with a heating pad.

Discontinue use of this product and consult a doctor if:

- Condition worsens
- Symptoms persist for more than 7 days or clear up and occur again within a few days
- Severe skin irritation occurs

If pregnant or breast-feeding, ask a health care professional before use

Keep out of reach of children. If swallowed, get medical help or contact a Poison Control immediately

Directions

- Roll generously to affected area 3-4 times daily
- Children under 12, consult a doctor before use.

Other information

Store in a cool dry place 20° to 25° C (68° to 77° F). This product may cause allergic reaction in some individuals. Test on small area before use. Do not use if seal is broken.

Inactive Ingredients

Borneol, Cassia Oil, Cinnamon Oil, Citronella Oil, Clove Oil, Coconut Oil, Light Liquid Paraffin, Narayani Oil, Nutmeg Oil, Peppermint Oil